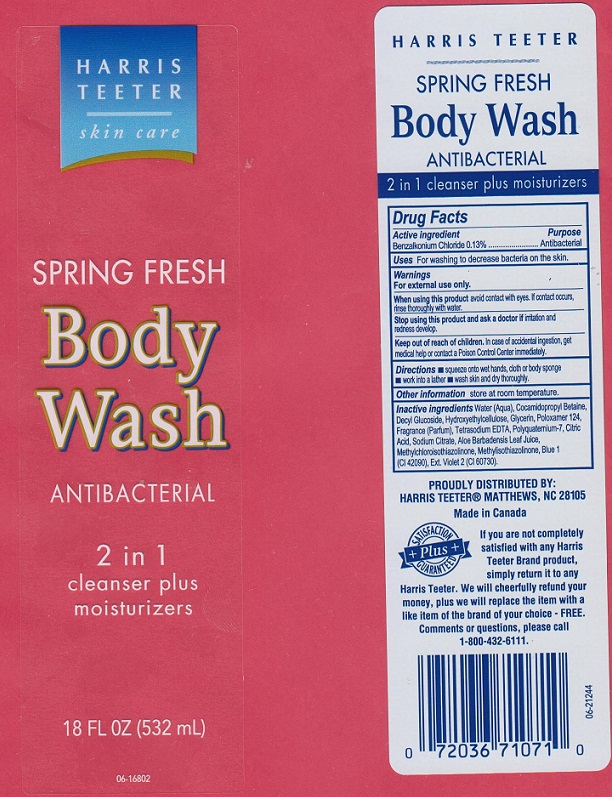 DRUG LABEL: Harris Teeter Spring Fresh Body Wash
NDC: 72036-801 | Form: LIQUID
Manufacturer: Harris Teeter
Category: otc | Type: HUMAN OTC DRUG LABEL
Date: 20180726

ACTIVE INGREDIENTS: BENZALKONIUM CHLORIDE 1.3 mg/1 mL
INACTIVE INGREDIENTS: WATER; COCAMIDOPROPYL BETAINE; DECYL GLUCOSIDE; HYDROXYETHYL CELLULOSE (5000 CPS AT 1%); GLYCERIN; POLOXAMER 124; EDETATE SODIUM; POLYQUATERNIUM-7 (70/30 ACRYLAMIDE/DADMAC; 1600000 MW); CITRIC ACID MONOHYDRATE; SODIUM CITRATE; ALOE VERA LEAF; METHYLCHLOROISOTHIAZOLINONE; METHYLISOTHIAZOLINONE; FD&C BLUE NO. 1; EXT. D&C VIOLET NO. 2

Drug Facts

Active ingredient

Benzalkonium Chloride 0.13%

Purpose

Antibacterial

Uses

For washing to decrease bacteria on the skin.

Warnings

For external use only.

When using this product

avoid contact with eyes. If contacct occurs, rinse thoroughly with water.

Stop using this product and ask a doctor if

irritation and redness develop.

Keep out of reach of children.

In case of accidental ingestion, get medical help or contact a Poison Control Center immediately.

Directions

- squeeze onto wet hands, cloth or body sponge
- work into a lather
- wash skin and dry thoroughly

Other information

store at room temperature.

Inactive ingredients

Water (Aqua), Cocamidopropyl Betaine, Decyl Glucoside, Hydroxyethylcellulose, Glycerin, Poloxamer 124, Fragrance (Parfum), Tetrasodium EDTA, Polyquaternium-7, Citric Acid, Sodium Citrate, Aloe Barbadensis Leaf Juice, Methylchloroisothiazolinone, Methylisothiazolinone, Blue 1 (CI 42090), Ext. Violet 2 (CI 60730).